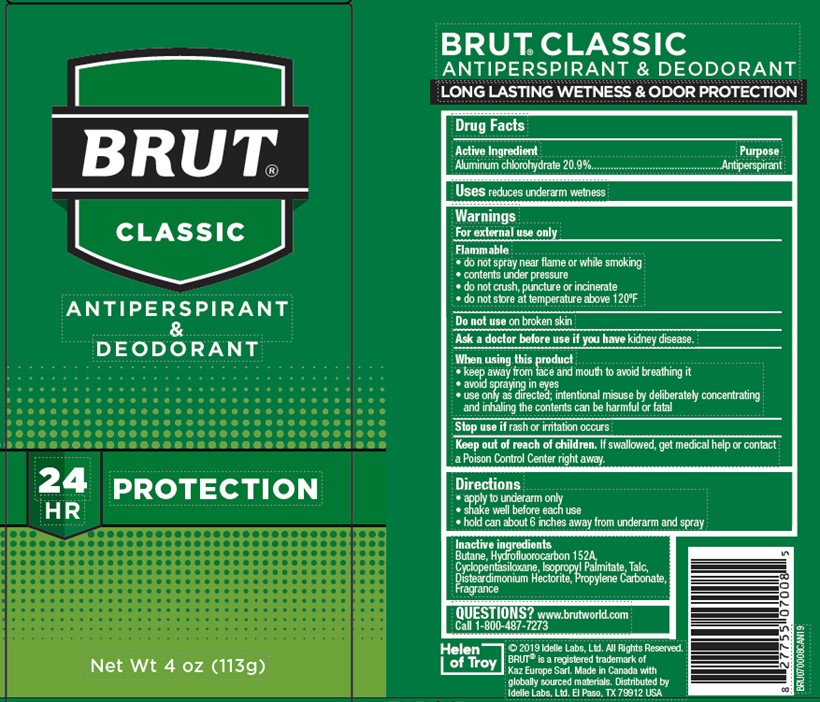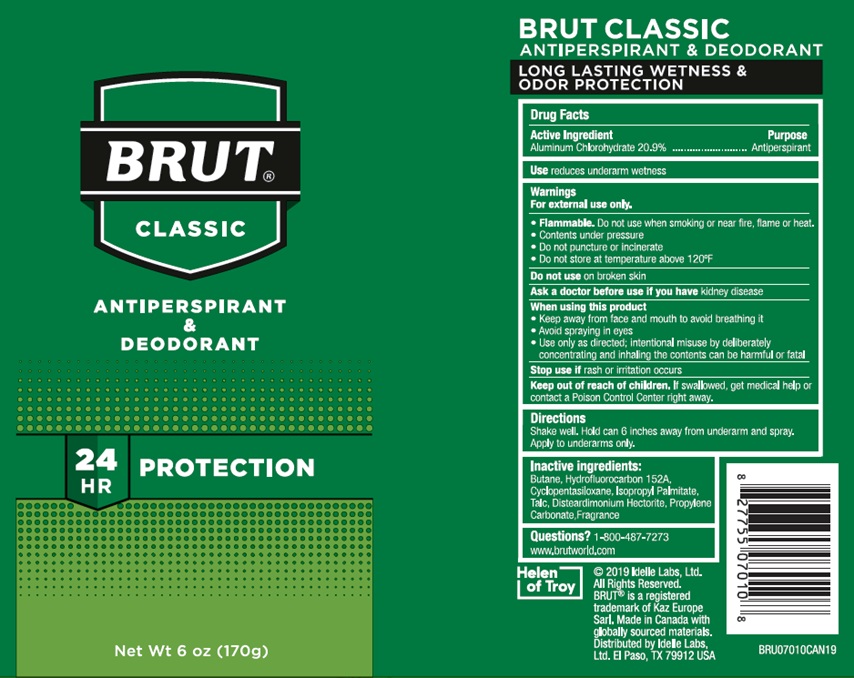 DRUG LABEL: Brut Classic Anti-perspirant and Deodorant
NDC: 41595-7103 | Form: AEROSOL
Manufacturer: Idelle Labs, Ltd
Category: otc | Type: HUMAN OTC DRUG LABEL
Date: 20210528

ACTIVE INGREDIENTS: ALUMINUM CHLOROHYDRATE 20.9 g/100 g
INACTIVE INGREDIENTS: BUTANE; CYCLOMETHICONE 5; DISTEARDIMONIUM HECTORITE; 1,1-DIFLUOROETHANE; ISOPROPYL PALMITATE; PROPYLENE CARBONATE; TALC

Brut Anti-perspirant and Deodorant 20.9%

Drug Facts

BRUT® ANTI-PERSPIRANT
& DEODORANT

LONG LASTING WETNESS & ODOR PROTECTION

Formulated with TRIMAX® to keep you dry and odor free.

Drug Facts

Active Ingredient

Aluminum chlorohydrate 20.9%

Purpose

Antiperspirant

Uses

Reduces underarm wetness

Warnings

For external use only

- Flammable do not use when smoking or near fire, flame or heat
- contents under pressure
- do not puncture or incinerate
- do not store at temperature above 120°F

Do not use

on broken skin

Ask a doctor before use

if you have kidney disease

When using this product

- Keep away from face and mouth to avoid breathing it
- avoid spraying in eyes
- use only as directed; intentional misuse by deliberately concentrating and inhaling the contents can be harmful or fatal

Stop use

if rash or irritation occurs

Keep out of reach of children

If swallowed, get medical help or contact a Poison Control Center right away.

Directions

Shake well. Hold can 6 inches away from underarm and spray. Apply to underarms only.

Inactive ingredients

Butane, hydrofluorocarbon 152A, cyclopentasiloxane, isopropyl palmitate, talc, disteardimonium hectorite, propylene carbonate, fragrance

Questions?

1-800-487-7273
www.brutworld.com

BRUT® CLASSIC

Antiperspirant & Deodorant

©2019 Idelle Labs, Ltd.

Made in Canada with globally sourced materials

Distributed by Idelle Labs, Ltd. El Paso, TX 79912 USA

Net Wt 6 oz (170 g)

Net Wt 4 oz (113 g)